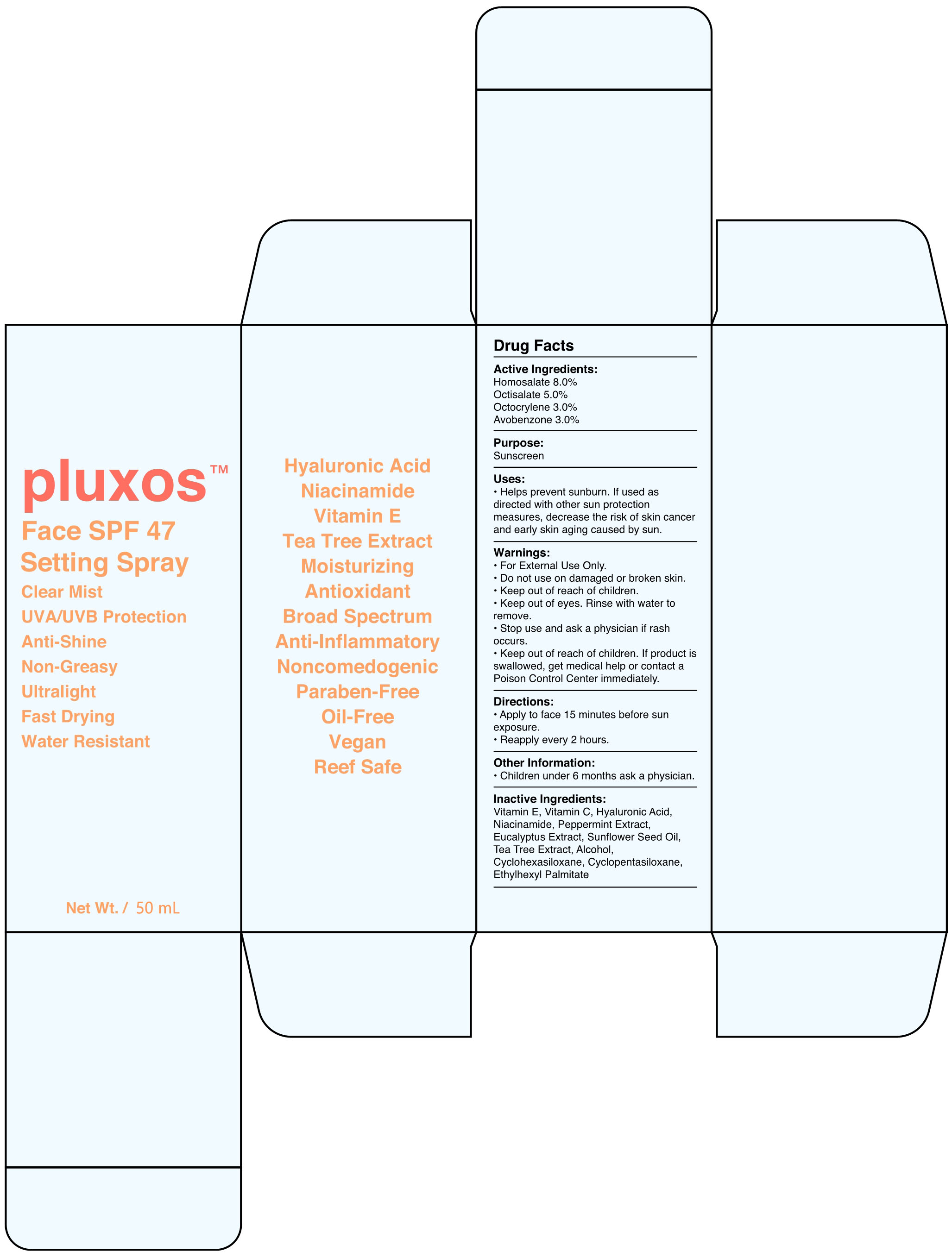 DRUG LABEL: FACE SPF 47 SETTING
NDC: 87283-001 | Form: SPRAY
Manufacturer: Aopline Biotechnology (Guangzhou) Co., Ltd.
Category: otc | Type: HUMAN OTC DRUG LABEL
Date: 20260108

ACTIVE INGREDIENTS: OCTOCRYLENE 3 g/100 mL; AVOBENZONE 3 g/100 mL; OCTISALATE 5 g/100 mL; HOMOSALATE 8 g/100 mL
INACTIVE INGREDIENTS: .ALPHA.-TOCOPHEROL; ALCOHOL; HYALURONIC ACID; EUCALYPTUS GLOBULUS LEAF; MELALEUCA ALTERNIFOLIA LEAF; SUNFLOWER OIL; CYCLOMETHICONE 6; NIACINAMIDE; PEPPERMINT; CYCLOMETHICONE 5; ETHYLHEXYL PALMITATE; ASCORBIC ACID

87283-001-01 FACE SPF 47 SETTING

ACTIVE INGREDIENT

Homosalate 8.0%

Octisalate 5.0%

Octocrylene 3.0%

Avobenzone 3.0%

PURPOSE

Sunscreen

Keep out of reach of children.

WARNINGS

For External Use Only.

Do not use on damaged or broken skin.

Keep out of reach of children.

Keep out of eyes. Rinse with water to remove.

Stop use and ask a physician if rash occurs.

Keep out of reach of children . If product is swallowed, get medical help or contact a Poison Control Center immediately.

DOSAGE AND ADMINISTRATION

•Apply to face 15 minutes before sun exposure.

Reapply every 2 hours.

INACTIVE INGREDIENT

Vitamin E, Vitamin C, Hyaluronic Acid, Niacinamide, Peppermint Extract, Eucalyptus Extract, Sunflower Seed Oil, Tea Tree Extract, Alcohol, Cyclohexasiloxane, Cyclopentasiloxane, Ethylhexyl Palmitate

INDICATIONS AND USAGE

Helps prevent sunburn. If used as directed with other sun protection measures, decrease the risk of skin cancer and early skin aging caused by sun.